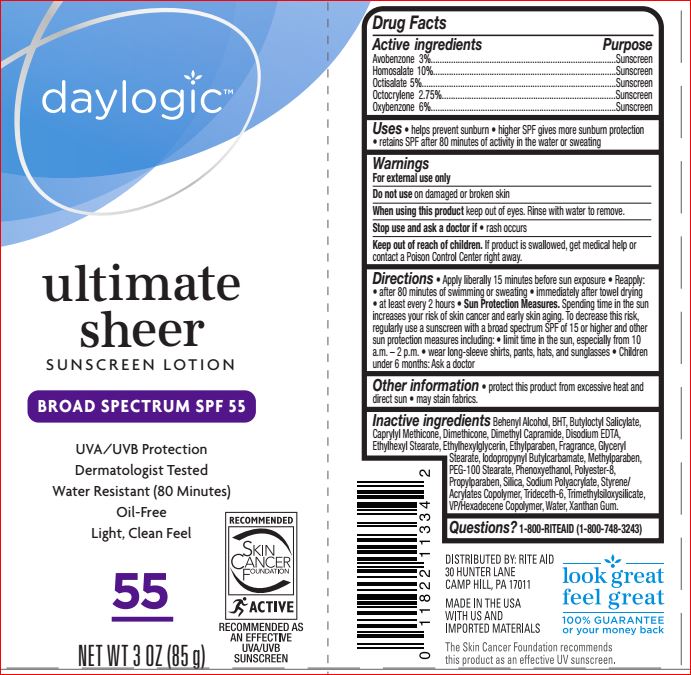 DRUG LABEL: Ultimate Seer Sunscreen SPF 55
NDC: 11822-1241 | Form: LOTION
Manufacturer: Rite Aid
Category: otc | Type: HUMAN OTC DRUG LABEL
Date: 20180720

ACTIVE INGREDIENTS: Avobenzone 3 g/100 mL; Homosalate 10 g/100 mL; Octisalate 5 g/100 mL; Octocrylene 2.75 g/100 mL; Oxybenzone 6 g/100 mL
INACTIVE INGREDIENTS: DOCOSANOL; BUTYLATED HYDROXYTOLUENE; Butyloctyl Salicylate; CAPRYLYL TRISILOXANE; Dimethicone; Dimethyl Capramide; EDETATE DISODIUM ANHYDROUS; Ethylhexyl Stearate; Ethylhexylglycerin; Ethylparaben; GLYCERYL MONOSTEARATE; Iodopropynyl Butylcarbamate; Methylparaben; PEG-100 Stearate; Phenoxyethanol; POLYESTER-8 (1400 MW, CYANODIPHENYLPROPENOYL CAPPED); Propylparaben; SILICON DIOXIDE; Trideceth-6; VINYLPYRROLIDONE/HEXADECENE COPOLYMER; WATER; Xanthan Gum

Drug Facts

Active ingredients Purpose

Avobenzone - 3.00% Sunscreen
Homosalate - 10.00% Sunscreen
Octisalate - 5.00% Sunscreen
Octocrylene - 2.75% Sunscreen
Oxybenzone - 6.00% Sunscreen

Uses

• helps prevent sunburn
• higher SPF gives more sunburn protection

Warnings For external use only

Do not use on damaged or broken skin
When using this product keep out of eyes. Rinse with water to remove.
Stop use and ask a doctor if rash occurs

KEEP OUT OF REACH OF CHILDREN

Keep out of reach of the children. If product is swallowed, get medical help or contact a Poison Control Center right away

Directions

• apply liberally 15 minutes before sun exposure
• reapply:
- after 80 minutes of swimming or sweating
- immediately after towel drying
- at least every 2 hours
• Sun Protection Measures. Spending time in the sun increases your risk of skin cancer and early skin aging. To decrease this risk, regularly use a sunscreen SPF of 15 or higher and other sun protection measures including:
- limit time in the sun, especially from 10 a.m. – 2 p.m.
- wear long sleeve shirts, pants, hats, and sunglasses
• children under 6 month: Ask a doctor

Inactive ingredients

Behenyl Alcohol, BHT, Butyloctyl Salicylate, Caprylyl Methicone, Dimethicone, Dimethyl Capramide, Disodium EDTA, Ethylhexyl Stearate,
Ethylhexylglycerin, Ethylparaben, Fragrance, Glyceryl Stearate, Iodopropynyl Butylcarbamate, Methylparaben, PEG-100 Stearate, Phenoxyethanol, Polyester-8, Propylparaben, Silica, Sodium Polyacrylate, Styrene/Acrylates Copolymer, Trideceth-6, Trimethylsiloxysilicate, VP/Hexadecene Copolymer, Water, Xanthan Gum

Other information

• protect this product from excessive heat and direct sun • may stain fabrics